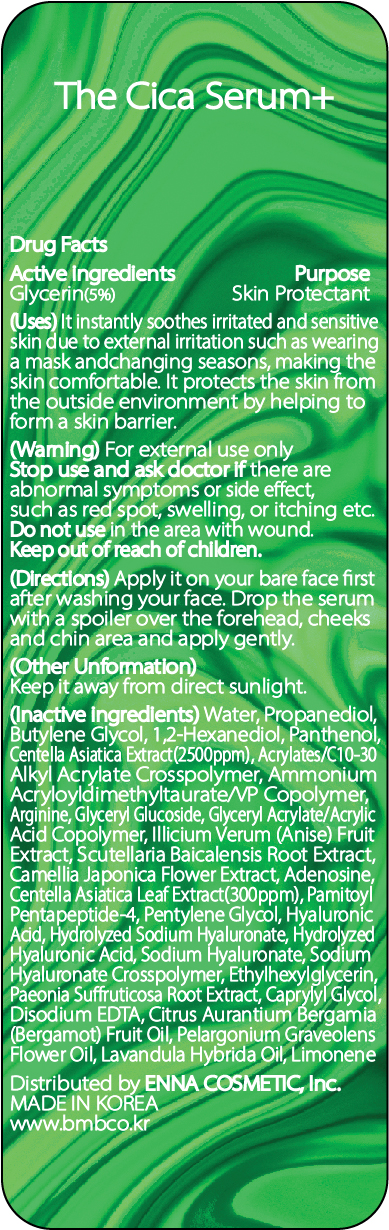 DRUG LABEL: The Cica Serum Plus
NDC: 81810-301 | Form: LOTION
Manufacturer: ENNA COSMETIC, Inc.
Category: otc | Type: HUMAN OTC DRUG LABEL
Date: 20230531

ACTIVE INGREDIENTS: GLYCERIN 5 mg/100 mL
INACTIVE INGREDIENTS: ETHYLHEXYLGLYCERIN; STAR ANISE FRUIT; PANTHENOL; AMMONIUM ACRYLOYLDIMETHYLTAURATE/VP COPOLYMER; ARGININE; CAMELLIA JAPONICA FLOWER; PENTYLENE GLYCOL; HYALURONATE SODIUM; EDETATE DISODIUM ANHYDROUS; ADENOSINE; CENTELLA ASIATICA LEAF; PALMITOYL PENTAPEPTIDE-4; PAEONIA SUFFRUTICOSA ROOT; CAPRYLYL GLYCOL; BERGAMOT OIL; PELARGONIUM GRAVEOLENS FLOWER OIL; LAVANDIN OIL; LIMONENE, (+)-; WATER; 1,2-HEXANEDIOL; CENTELLA ASIATICA; PROPANEDIOL; BUTYLENE GLYCOL; SCUTELLARIA BAICALENSIS ROOT; HYALURONIC ACID

81810-301 The Cica Serum Plus

Active ingredients

Glycerin(5%)

Purpose

Skin Protectant

Uses

It instantly soothes irritated and sensitive skin due to external irritation such as wearing a mask and changing seasons, making the skin comfortable. It protects the skin from the outside environment by helping to form a skin barrier.

Warning

For external use only

Stop use and ask doctor if

there are abnormal symptoms or side effects, such as red spot, swelling, or itching etc.

Do not use

in the area with wound.

Keep out of reach of children

Directions

Apply it on your bare face first after washing your face, Drop the serum with a spoiler over the forehead, cheeks and chin area and apply gently.

Other Information

Keep it away from direct sunlight.

Inactive ingredients

Water, Propanediol, Butylene Glycol, 1,2-Hexanediol, Panthenol, Centella Asiatica Extract(2500ppm), Acrylates/C10-30 Alkyl Acrylate Crosspolymer, Ammonium Acryloyldimethyltaurate/VP Copolymer, Arginine, Glyceryl Glucoside, Glyceryl Acrylate/Acrylic Acid Copolymer, Illicium Verum (Anise) Fruit Extract, Scutellaria Baicalensis Root Extract, Camellia Japonica Flower Extract, Adenosine, Centella Asiatica Leaf Extract(300ppm), Pamitoyl Pentapeptide-4, Pentylene Glycol, Hyaluronic Acid, Hydrolyzed Sodium Hyaluronate, Hydrolyzed Hyaluronic Acid, Sodium Hyaluronate, Sodium Hyaluronate Crosspolymer, Ethylhexylglycerin, Paeonia Suffruticosa Root Extract, Caprylyl Glycol, Disodium EDTA, Citrus Aurantium Bergamia (Bergamot) Fruit Oil, Pelargonium Graveolens Flower Oil, Lavandula Hybrida Oil, Limonene